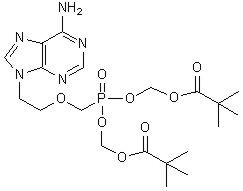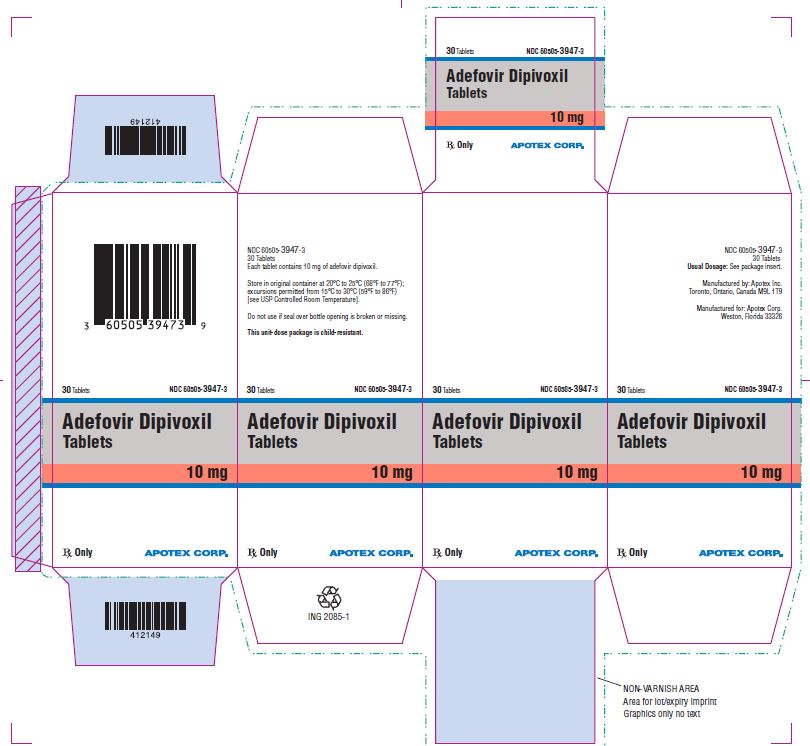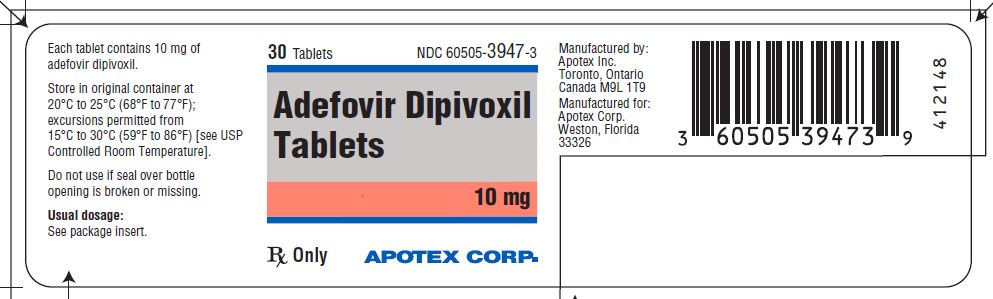 DRUG LABEL: Adefovir dipivoxil
NDC: 60505-3947 | Form: TABLET
Manufacturer: Apotex Corp.
Category: prescription | Type: HUMAN PRESCRIPTION DRUG LABEL
Date: 20250722

ACTIVE INGREDIENTS: ADEFOVIR DIPIVOXIL 10 mg/1 1
INACTIVE INGREDIENTS: STARCH, CORN; CROSCARMELLOSE SODIUM; LACTOSE MONOHYDRATE; TALC; MAGNESIUM STEARATE

HIGHLIGHTS OF PRESCRIBING INFORMATION

These highlights do not include all the information needed to use ADEFOVIR DIPIVOXIL TABLETS safely and effectively. See full prescribing information for ADEFOVIR DIPIVOXIL TABLETS.
ADEFOVIR DIPIVOXIL tablets, for oral use
Initial U.S. Approval: 2002

WARNING: SEVERE ACUTE EXACERBATIONS OF HEPATITIS, NEPHROTOXICITY, HIV RESISTANCE, LACTIC ACIDOSIS AND SEVERE HEPATOMEGALY WITH STEATOSIS

See full prescribing information for complete boxed warning.

- Severe acute exacerbations of hepatitis may occur in patients who discontinue adefovir dipivoxil tablets. Monitor hepatic function closely in these patients. (5.1)
- Chronic use of adefovir dipivoxil tablets may result in nephrotoxicity in patients at risk of renal dysfunction or having underlying renal dysfunction. Monitor renal function closely in these patients. Dose adjustment may be required. (5.2)
- HIV resistance may emerge in chronic hepatitis B patients with unrecognized or untreated HIV infection. (5.3)
- Lactic acidosis and severe hepatomegaly with steatosis, including fatal cases, have been reported with the use of nucleoside analogues. (5.4)

1 INDICATIONS AND USAGE

Adefovir dipivoxil tablets are a nucleotide analogue indicated for the treatment of chronic hepatitis B in patients 12 years of age and older. (1)

2 DOSAGE AND ADMINISTRATION

- One tablet containing 10 mg adefovir dipivoxil once daily orally with or without food. (2.1)
- Dose adjustment in renal impairment for adults (2.2)

 | Creatinine Clearance (mL/min) [Creatinine clearance calculated by Cockcroft-Gault method using lean or ideal body weight.]
 | Greater than or equal to 50 | 30 to 49 | 10 to 29 | Hemodialysis Patients
Recommended dose and dosing interval | 10 mg every 24 hours | 10 mg every 48 hours | 10 mg every 72 hours | 10 mg every 7 days following dialysis

- No dose recommendations for (2.1):
  - Non-hemodialysis patients with creatinine clearance less than 10 mL per minute.
  - Adolescent patients with renal impairment.

3 DOSAGE FORMS AND STRENGTHS

Tablets: 10 mg (3)

4 CONTRAINDICATIONS

Adefovir dipivoxil tablets are contraindicated in patients with previously demonstrated hypersensitivity to any of the components of the product. (4)

5 WARNINGS AND PRECAUTIONS

- Severe acute exacerbations of hepatitis: Monitor hepatic function closely at repeated intervals for at least several months in patients who discontinue adefovir dipivoxil. (5.1)
- Nephrotoxicity: Monitor renal function during therapy for all patients, particularly those with pre-existing or other risks for renal impairment. Dose adjustment may be required. (5.2)
- HIV Resistance: Offer HIV testing to all patients prior to initiating adefovir dipivoxil. Untreated HIV may result in HIV resistance. (5.3)
- Lactic acidosis and severe hepatomegaly with steatosis: If suspected, suspend treatment. (5.4)
- Coadministration with Other Products: Do not administer adefovir dipivoxil concurrently with VIREAD® or other tenofovir-containing products. (5.5)
- Clinical Resistance: For patients with lamivudine-resistant HBV use adefovir dipivoxil in combination with lamivudine. For all patients, consider modifying treatment in case serum HBV DNA remains above 1000 copies/mL with continued treatment. (5.6)

6 ADVERSE REACTIONS

Most common adverse reaction (incidence greater than 5%) in compensated liver disease patients were asthenia, headache, abdominal pain and nausea. (6.1) The most common adverse reaction in pre- and post- transplantation lamivudine-resistant liver disease patients was increased creatinine. (6.2)

To report SUSPECTED ADVERSE REACTIONS, contact Apotex Corp. at 1-800-706-5575or FDA at 1-800-FDA-1088 or www.fda.gov/medwatch.

7 DRUG INTERACTIONS

Coadministration with drugs that reduce renal function or compete for active tubular secretion may increase serum concentrations of adefovir or the coadministered drug. Monitor for adefovir dipivoxil associated adverse events. (7)

8 USE IN SPECIFIC POPULATIONS

- • Pediatrics: Not recommended in children less than 12 years of age. (2.1, 8.4,14.4)
- Renal Impairment: Dose adjustment may be required. (2.2)

FULL PRESCRIBING INFORMATION

WARNING: SEVERE ACUTE EXACERBATIONS OF HEPATITIS, NEPHROTOXICITY, HIV RESISTANCE, LACTIC ACIDOSIS AND SEVERE HEPATOMEGALY WITH STEATOSIS

Severe acute exacerbations of hepatitis have been reported in patients who have discontinued anti-Hepatitis B therapy including adefovir dipivoxil tablets. Hepatic function should be monitored closely with both clinical and laboratory follow-up for at least several months in patients who discontinue anti-Hepatitis B therapy. If appropriate, resumption of anti-Hepatitis B therapy may be warranted [See Warnings and Precautions (5.1)].

In patients at risk of or having underlying renal dysfunction, chronic administration of adefovir dipivoxil tablets may result in nephrotoxicity. These patients should be monitored closely for renal function and may require dose adjustment [See Warnings and Precautions (5.2) and Dosage and Administration (2.2)].

HIV resistance may emerge in chronic hepatitis B patients with unrecognized or untreated Human Immunodeficiency Virus (HIV) infection treated with anti-hepatitis B therapies, such as therapy with adefovir dipivoxil tablets, that may have activity against HIV [See Warnings and Precautions (5.3)].

Lactic acidosis and severe hepatomegaly with steatosis, including fatal cases, have been reported with the use of nucleoside analogs alone or in combination with other antiretrovirals [See Warnings and Precautions (5.4)].

1 INDICATIONS AND USAGE

Adefovir dipivoxil tablets are indicated for the treatment of chronic hepatitis B in patients 12 years of age and older with evidence of active viral replication and either evidence of persistent elevations in serum aminotransferases (ALT or AST) or histologically active disease.

This indication is based on histological, virological, biochemical, and serological responses in adult patients with HBeAg+ and HBeAg- chronic hepatitis B with compensated liver function, and with clinical evidence of lamivudine-resistant hepatitis B virus with either compensated or decompensated liver function.

For patients 12 to less than 18 years of age, the indication is based on virological and biochemical responses in patients with HBeAg+ chronic hepatitis B virus infection with compensated liver function.

2 DOSAGE AND ADMINISTRATION

2.1 Chronic Hepatitis B

The recommended dose of adefovir dipivoxil tablets in chronic hepatitis B patients for patients 12 years of age and older with adequate renal function is 10 mg, once daily, taken orally, without regard to food. The optimal duration of treatment is unknown.

Adefovir dipivoxil tablets are not recommended for use in children less than 12 years of age.

2.2 Dose Adjustment in Renal Impairment

Significantly increased drug exposures were seen when adefovir dipivoxil tablets were administered to adult patients with renal impairment [See Warnings and Precautions (5.2) and Clinical Pharmacology (12.3)]. Therefore, the dosing interval of adefovir dipivoxil tablets should be adjusted in adult patients with baseline creatinine clearance less than 50 mL per minute using the following suggested guidelines (See Table 1). The safety and effectiveness of these dosing interval adjustment guidelines have not been clinically evaluated.

Additionally, it is important to note that these guidelines were derived from data in patients with pre-existing renal impairment at baseline. They may not be appropriate for patients in whom renal insufficiency evolves during treatment with adefovir dipivoxil tablets. Therefore, clinical response to treatment and renal function should be closely monitored in these patients.

Table 1 Dosing Interval Adjustment of Adefovir Dipivoxil Tablets in Adult Patients with Renal Impairment
 | Creatinine Clearance (mL/min) [Creatinine clearance calculated by Cockcroft-Gault method using lean or ideal body weight.]
 | Greater than or equal to 50 | 30 to 49 | 10 to 29 | Hemodialysis Patients
Recommended dose and dosing interval | 10 mg every 24 hours | 10 mg every 48 hours | 10 mg every 72 hours | 10 mg every 7 days following dialysis

The pharmacokinetics of adefovir have not been evaluated in non-hemodialysis patients with creatinine clearance less than 10 mL per minute; therefore, no dosing recommendation is available for these patients.

No clinical data are available to make dosing recommendations in adolescent patients with renal insufficiency [See Warnings and Precautions (5.2)].

3 DOSAGE FORMS AND STRENGTHS

Adefovir Dipivoxil Tablets are white to off-white, round, flat-faced bevelled edge tablets, engraved “APO” on one side, “A10” on the other side.

4 CONTRAINDICATIONS

Adefovir dipivoxil tablets are contraindicated in patients with previously demonstrated hypersensitivity to any of the components of the product.

5 WARNINGS AND PRECAUTIONS

5.1 Exacerbation of Hepatitis after Discontinuation of Treatment

Severe acute exacerbation of hepatitis has been reported in patients who have discontinued anti-hepatitis B therapy, including therapy with adefovir dipivoxil. Hepatic function should be monitored at repeated intervals with both clinical and laboratory follow-up for at least several months in patients who discontinue adefovir dipivoxil. If appropriate, resumption of anti-hepatitis B therapy may be warranted.

In clinical trials of adefovir dipivoxil, exacerbations of hepatitis (ALT elevations 10 times the upper limit of normal or greater) occurred in up to 25% of patients after discontinuation of adefovir dipivoxil. These events were identified in studies GS-98-437 and GS-98-438 (N=492). Most of these events occurred within 12 weeks of drug discontinuation. These exacerbations generally occurred in the absence of HBeAg seroconversion, and presented as serum ALT elevations in addition to re-emergence of viral replication. In the HBeAg-positive and HBeAg-negative studies in patients with compensated liver function, the exacerbations were not generally accompanied by hepatic decompensation. However, patients with advanced liver disease or cirrhosis may be at higher risk for hepatic decompensation. Although most events appear to have been self-limited or resolved with re-initiation of treatment, severe hepatitis exacerbations, including fatalities, have been reported. Therefore, patients should be closely monitored after stopping treatment.

5.2 Nephrotoxicity

Nephrotoxicity characterized by a delayed onset of gradual increases in serum creatinine and decreases in serum phosphorus was historically shown to be the treatment-limiting toxicity of adefovir dipivoxil therapy at substantially higher doses in HIV-infected patients (60 and 120 mg daily) and in chronic hepatitis B patients (30 mg daily). Chronic administration of adefovir dipivoxil (10 mg once daily) may result in delayed nephrotoxicity. The overall risk of nephrotoxicity in patients with adequate renal function is low. However, this is of special importance in patients at risk of or having underlying renal dysfunction and patients taking concomitant nephrotoxic agents such as cyclosporine, tacrolimus, aminoglycosides, vancomycin and non-steroidal anti-inflammatory drugs [See Adverse Reactions (6.2) and Clinical Pharmacology (12.3)]. It is recommended that creatinine clearance is calculated in all patients prior to initiating therapy with adefovir dipivoxil.

It is important to monitor renal function for all patients during treatment with adefovir dipivoxil, particularly for those with pre-existing or other risks for renal impairment. Patients with renal insufficiency at baseline or during treatment may require dose adjustment [See Dosage and Administration (2.2)]. The risks and benefits of adefovir dipivoxil treatment should be carefully evaluated prior to discontinuing adefovir dipivoxil in a patient with treatment-emergent nephrotoxicity.

Pediatric Patients

The efficacy and safety of adefovir dipivoxil have not been studied in patients less than 18 years of age with different degrees of renal impairment and no data are available to make dosage recommendations in these patients [See Dosage and Administration (2.2)]. Caution should be exercised when prescribing adefovir dipivoxil to adolescents with underlying renal dysfunction, and renal function in these patients should be closely monitored.

5.3 HIV Resistance

Prior to initiating adefovir dipivoxil therapy, HIV antibody testing should be offered to all patients. Treatment with anti-hepatitis B therapies, such as adefovir dipivoxil, that have activity against HIV in a chronic hepatitis B patient with unrecognized or untreated HIV infection may result in emergence of HIV resistance. Adefovir dipivoxil has not been shown to suppress HIV RNA in patients; however, there are limited data on the use of adefovir dipivoxil to treat patients with chronic hepatitis B co-infected with HIV.

5.4 Lactic Acidosis/Severe Hepatomegaly with Steatosis

Lactic acidosis and severe hepatomegaly with steatosis, including fatal cases, have been reported with the use of nucleoside analogs alone or in combination with antiretrovirals.

A majority of these cases have been in women. Obesity and prolonged nucleoside exposure may be risk factors. Particular caution should be exercised when administering nucleoside analogs to any patient with known risk factors for liver disease; however, cases have also been reported in patients with no known risk factors. Treatment with adefovir dipivoxil should be suspended in any patient who develops clinical or laboratory findings suggestive of lactic acidosis or pronounced hepatotoxicity (which may include hepatomegaly and steatosis even in the absence of marked transaminase elevations).

5.5 Coadministration with Other Products

Adefovir dipivoxil should not be used concurrently with products containing tenofovir disoproxil fumarate or tenofovir alafenamide.

5.6 Clinical Resistance

Resistance to adefovir dipivoxil can result in viral load rebound which may result in exacerbation of hepatitis B and, in the setting of diminished hepatic function, lead to liver decompensation and possible fatal outcome.

In order to reduce the risk of resistance in patients with lamivudine resistant HBV, adefovir dipivoxil should be used in combination with lamivudine and not as adefovir dipivoxil monotherapy.

In order to reduce the risk of resistance in all patients receiving adefovir dipivoxil monotherapy, a modification of treatment should be considered if serum HBV DNA remains above 1000 copies/mL with continued treatment.

Long-term (144 week) data from Study 438 (N=124) show that patients with HBV DNA levels greater than 1000 copies/mL at Week 48 of treatment with adefovir dipivoxil were at greater risk of developing resistance than patients with serum HBV DNA levels below 1000 copies/mL at Week 48 of therapy.

6 ADVERSE REACTIONS

The following adverse reactions are discussed in other sections of the labeling:

- Severe acute exacerbations of Hepatitis [See Boxed Warning, Warnings and Precautions (5.1)]
- Nephrotoxicity [See Boxed Warning, Warnings and Precautions (5.2)]

6.1 Clinical Trials Experience

Because clinical trials are conducted under widely varying conditions, adverse reaction rates observed in the clinical trials of a drug cannot be directly compared to rates in the clinical trials of another drug and may not reflect the rates observed in practice.

Clinical and laboratory evidence of exacerbations of hepatitis have occurred after discontinuation of treatment with adefovir dipivoxil.

Adverse reactions to adefovir dipivoxil identified from placebo-controlled and open label studies include the following: asthenia, headache, abdominal pain, diarrhea, nausea, dyspepsia, flatulence, increased creatinine, and hypophosphatemia.

The incidence of these adverse reactions in studies 437 and 438, where 522 patients with chronic hepatitis B and compensated liver disease received double-blind treatment with adefovir dipivoxil (N=294) or placebo (N=228) for 48 weeks is presented in Table 2. Patients who received open-label adefovir dipivoxil for up to 240 weeks in Study 438 reported adverse reactions similar in nature and severity to those reported in the first 48 weeks.

Table 2 Adverse Reactions (Grades 1 to 4) Reported in ≥3% of All Adefovir Dipivoxil-Treated Patients in Pooled Studies 437 to 438 Studies (0 to 48 Weeks) [In these studies, the overall incidence of adverse reactions with adefovir dipivoxil was similar to that reported with placebo. The incidence of adverse reactions is derived from treatment-related events as identified by the study investigators.]
Adverse Reaction | Adefovir Dipivoxil 10 mg (N=294) | Placebo (N=228)
Asthenia | 13% | 14%
Headache | 9% | 10%
Abdominal Pain | 9% | 11%
Nausea | 5% | 8%
Flatulence | 4% | 4%
Diarrhea | 3% | 4%
Dyspepsia | 3% | 2%

No patients treated with adefovir dipivoxil developed a confirmed serum creatinine increase greater than or equal to 0.5 mg/dL from baseline or a confirmed phosphorus decrease to 2 mg/dL or less by Week 48. By Week 96, 2% of adefovir dipivoxil-treated patients, by Kaplan-Meier estimate, had increases in serum creatinine greater than or equal to 0.5 mg/dL from baseline (no placebo-controlled results were available for comparison beyond Week 48). For patients who chose to continue adefovir dipivoxil for up to 240 weeks in Study 438, 4 of 125 patients (3%) had a confirmed increase of 0.5 mg/dL from baseline. The creatinine elevation resolved in 1 patient who permanently discontinued treatment and remained stable in 3 patients who continued treatment. For 65 patients who chose to continue adefovir dipivoxil for up to 240 weeks in Study 437, 6 had a confirmed increase in serum creatinine of greater than or equal to 0.5 mg/dL from baseline with 2 patients discontinuing from the study due to the elevated serum creatinine concentration. See Adverse Reactions (6.2) for changes in serum creatinine in patients with underlying renal insufficiency at baseline.

6.2 Special Risk Patients

Pre- and Post-Liver Transplantation Patients

Additional adverse reactions observed from an open-label study (Study 435) in pre- and post-liver transplantation patients with chronic hepatitis B and lamivudine-resistant hepatitis B administered adefovir dipivoxil once daily for up to 203 weeks include: abnormal renal function, renal failure, vomiting, rash, and pruritus.

Changes in renal function occurred in pre-and post-liver transplantation patients with risk factors for renal dysfunction, including concomitant use of cyclosporine and tacrolimus, renal insufficiency at baseline, hypertension, diabetes, and on-study transplantation. Therefore, the contributory role of adefovir dipivoxil to these changes in renal function is difficult to assess.

Increases in serum creatinine greater than or equal to 0.3 mg/dL from baseline were observed in 37% and 53% of pre-liver transplantation patients by Weeks 48 and 96, respectively, by Kaplan-Meier estimates. Increases in serum creatinine greater than or equal to 0.3 mg/dL from baseline were observed in 32% and 51% of post-liver transplantation patients by Weeks 48 and 96, respectively, by Kaplan-Meier estimates. Serum phosphorus values less than 2 mg/dL were observed in 3/226 (1.3%) of pre-liver transplantation patients and in 6/241 (2.5%) of post-liver transplantation patients by last study visit. Four percent (19 of 467) of patients discontinued treatment with adefovir dipivoxil due to renal adverse events.

6.3 Pediatric Patients

Assessment of adverse reactions is based on a placebo-controlled study (Study 518) in which 173 pediatric patients aged 2 to less than 18 years with chronic hepatitis B and compensated liver disease received double-blind treatment with adefovir dipivoxil (N=115), or placebo (N=58) for 48 weeks [See Clinical Studies (14.4) and Use In Specific Populations (8.4)].

The safety profile of adefovir dipivoxil in patients 12 to less than 18 years of age (N=56) was similar to that observed in adults. No pediatric patients treated with adefovir dipivoxil developed a confirmed serum creatinine increase greater than or equal to 0.5 mg/dL from baseline or a confirmed phosphorus decrease to less than 2 mg/dL by Week 48.

6.4 Post-Marketing Experience

In addition to adverse reaction reports from clinical trials, the following possible adverse reactions have also been identified during post-approval use of adefovir dipivoxil. Because these events have been reported voluntarily from a population of unknown size, estimates of frequency cannot be made.

Metabolism and Nutrition Disorders: hypophosphatemia

Gastrointestinal Disorders: pancreatitis

Musculoskeletal System and Connective Tissue Disorders: myopathy, osteomalacia (manifested as bone pain and may contribute to fractures), both associated with proximal renal tubulopathy

Renal and Urinary Disorders: renal failure, Fanconi syndrome, proximal renal tubulopathy

7 DRUG INTERACTIONS

Since adefovir is eliminated by the kidney, coadministration of adefovir dipivoxil with drugs that reduce renal function or compete for active tubular secretion may increase serum concentrations of either adefovir and/or these coadministered drugs [See Clinical Pharmacology (12.3)].

Patients should be monitored closely for adverse events when adefovir dipivoxil is coadministered with drugs that are excreted renally or with other drugs known to affect renal function [See Warnings and Precautions (5.2)].

Adefovir dipivoxil should not be administered in combination with VIREAD [See Warnings and Precautions (5.5)].

8 USE IN SPECIFIC POPULATIONS

8.1 Pregnancy

Pregnancy Exposure Registry

There is a pregnancy exposure registry that monitors pregnancy outcomes in women exposed to adefovir dipivoxil during pregnancy. Healthcare providers are encouraged to register patients by calling the Antiretroviral Pregnancy Registry (APR) at 1-800-258- 4263.

Risk Summary

Prospective pregnancy data from the APR are not sufficient to adequately assess the risk of birth defects, miscarriage or adverse maternal or fetal outcomes. Adefovir disoproxil (ADV) use during pregnancy has been evaluated in a limited number of individuals reported to the APR and the number of exposures to adefovir is insufficient to make a risk assessment compared to a reference population. The estimated background rate for major birth defects is 2.7% in the U.S. reference population of the Metropolitan Atlanta Congenital Defects Program (MACDP). The estimated rate of miscarriage is not reported in the APR. All pregnancies have a background risk of birth defect, loss, or other adverse outcomes. The estimated background rate of miscarriage in the U.S. general population is 15–20%.

In animal reproduction studies with oral ADV, no adverse developmental effects were observed at exposures (Cmax) 23 times higher in rats and 40 times higher in rabbits than those at the recommended human dose (RHD) of adefovir dipivoxil (see Data).

Data

Animal Data

In an embryo-fetal development study, ADV was administered orally to pregnant rabbits (at 1, 5, or 20 mg/kg/day) during organogenesis (on gestation day 6 through 18). No adverse developmental effects were observed at up to the highest dose tested, at systemic exposure (Cmax) 40 times that in humans at the RHD of adefovir dipivoxil.

In a pre/post-natal development study, ADV was administered orally to pregnant rats (at 2.5, 10, or 40 mg/kg/day) from organogenesis, through late gestation, delivery, and lactation (gestation day 7 to lactation/postpartum day 20). Reduced body weight of the offspring due to maternal toxicity was observed at systemic exposure 23 times that in humans at the RHD of adefovir dipivoxil.

In an embryo-fetal development study, ADV was administered intravenously to pregnant rats (at 2.5, 10, and 20 mg/kg/day) during organogenesis (gestation day 6 through 15). Embryo-fetal toxicity including malformations (anasarca, depressed eye bulge, umbilical hernia and kinked tail) and skeletal variations (reduction of ossified metacarpal bones, increases in thoracic vertebrae and decreases in lumbar vertebrae) occurred at systemic exposure (Cmax) 38 times that in humans at the RHD of adefovir dipivoxil. No adverse developmental effects were observed at an exposure (Cmax) 12 times that in humans at the RHD of adefovir dipivoxil.

8.2 Lactation

Risk Summary

It is not known whether adefovir is present in human breast milk, affects human milk production, or has effects on the breastfed infant.

The developmental and health benefits of breastfeeding should be considered along with the mother’s clinical need for adefovir dipivoxil and any potential adverse effects on the breastfed infant from adefovir dipivoxil or from the underlying maternal condition.

8.4 Pediatric Use

Pediatric patients 12 to less than 18 years: The safety, efficacy, and pharmacokinetics of adefovir dipivoxil in pediatric patients (aged 12 to less than 18 years) were evaluated in a double-blind, randomized, placebo-controlled study (GS-US-103-518, Study 518) in 83 pediatric patients with chronic hepatitis B and compensated liver disease. The proportion of patients treated with adefovir dipivoxil who achieved the primary efficacy endpoint of serum HBV DNA less than 1,000 copies/mL and normal ALT levels at the end of 48 weeks blinded treatment was significantly greater (23%) when compared to placebo-treated patients (0%) [See Clinical Studies (14.4), Dosage and Administration (2) and Adverse Reactions (6.3)].

Pediatric patients 2 to less than 12 years: Patients 2 to less than 12 years of age were also evaluated in Study 518. The efficacy of adefovir dipivoxil was not significantly different from placebo in patients less than 12 years of age.

Adefovir dipivoxil tablets are not recommended for use in children below 12 years of age.

8.5 Geriatric Use

Clinical studies of adefovir dipivoxil did not include sufficient numbers of patients aged 65 and over to determine whether they respond differently from younger patients. In general, caution should be exercised when prescribing to elderly patients since they have greater frequency of decreased renal or cardiac function due to concomitant disease or other drug therapy.

8.6 Patients with Impaired Renal Function

It is recommended that the dosing interval for adefovir dipivoxil be modified in adult patients with baseline creatinine clearance less than 50 mL per minute. The pharmacokinetics of adefovir have not been evaluated in non-hemodialysis patients with creatinine clearance less than 10 mL per minute or in adolescent patients with renal insufficiency; therefore, no dosing recommendations are available for these patients [See Dosage and Administration (2.2) and Warnings and Precautions (5.2)].

10 OVERDOSAGE

Doses of adefovir dipivoxil 500 mg daily for 2 weeks and 250 mg daily for 12 weeks have been associated with gastrointestinal side effects. If overdose occurs the patient must be monitored for evidence of toxicity, and standard supportive treatment applied as necessary.

Following a 10 mg single dose of adefovir dipivoxil, a four-hour hemodialysis session removed approximately 35% of the adefovir dose.

11 DESCRIPTION

Adefovir dipivoxil is a diester prodrug of adefovir. Adefovir is an acyclic nucleotide analog with activity against human hepatitis B virus (HBV).

The chemical name of adefovir dipivoxil is 9-[2-[[bis[(pivaloyloxy)methoxy]-phosphinyl]-methoxy]ethyl]adenine. It has a molecular formula of C20H32N5O8P, a molecular weight of 501.47 g/mol and the following structural formula:

Adefovir dipivoxil is a white to off-white powder with an aqueous solubility of 19 mg/mL at pH 2.0 and 0.4 mg/mL at pH 7.2. It has an octanol/aqueous phosphate buffer (pH 7) partition coefficient (log p) of 1.91.

Adefovir dipivoxil tablets are for oral administration. Each tablet contains 10 mg of adefovir dipivoxil and the following inactive ingredients: croscarmellose sodium, lactose monohydrate, magnesium stearate, starch and talc.

12 CLINICAL PHARMACOLOGY

12.1 Mechanism of Action

Adefovir is an antiviral drug [See Microbiology (12.4)].

12.3 Pharmacokinetics

Adult Subjects

The pharmacokinetics of adefovir have been evaluated in healthy volunteers and patients with chronic hepatitis B. Adefovir pharmacokinetics are similar between these populations.

Absorption

Adefovir dipivoxil is a diester prodrug of the active moiety adefovir. Based on a cross study comparison, the approximate oral bioavailability of adefovir from adefovir dipivoxil is 59%.

Following oral administration of a 10 mg single dose of adefovir dipivoxil to chronic hepatitis B patients (N=14), the peak adefovir plasma concentration (Cmax) was 18.4 ± 6.26 ng/mL (mean ± SD) and occurred between 0.58 and 4.00 hours (median = 1.75 hours) post dose. The adefovir area under the plasma concentration-time curve (AUC0–∞) was 220 ± 70.0 ng•h/mL. Plasma adefovir concentrations declined in a biexponential manner with a terminal elimination half-life of 7.48 ± 1.65 hours.

The pharmacokinetics of adefovir in subjects with adequate renal function were not affected by once daily dosing of 10 mg adefovir dipivoxil over seven days. The impact of long-term once daily administration of 10 mg adefovir dipivoxil on adefovir pharmacokinetics has not been evaluated.

Effects of Food on Oral Absorption

Adefovir exposure was unaffected when a 10 mg single dose of adefovir dipivoxil was administered with food (an approximately 1000 kcal high-fat meal). Adefovir dipivoxil may be taken without regard to food.

Distribution

In vitro binding of adefovir to human plasma or human serum proteins is less than or equal to 4% over the adefovir concentration range of 0.1 to 25 microg/mL. The volume of distribution at steady-state following intravenous administration of 1.0 or 3.0 mg/kg/day is 392 ± 75 and 352 ± 9 mL/kg, respectively.

Metabolism and Elimination

Following oral administration, adefovir dipivoxil is rapidly converted to adefovir. Forty-five percent of the dose is recovered as adefovir in the urine over 24 hours at steady state following 10 mg oral doses of adefovir dipivoxil. Adefovir is renally excreted by a combination of glomerular filtration and active tubular secretion [See Drug Interactions (7) and Clinical Pharmacology (12.3)].

Assessment of Drug Interactions

Adefovir dipivoxil is rapidly converted to adefovir in vivo. At concentrations substantially higher (greater than 4000-fold) than those observed in vivo, adefovir did not inhibit any of the common human CYP450 enzymes, CYP1A2, CYP2C9, CYP2C19, CYP2D6, and CYP3A4. Adefovir is not a substrate for these enzymes. However, the potential for adefovir to induce CYP450 enzymes is unknown. Based on the results of these in vitro experiments and the renal elimination pathway of adefovir, the potential for CYP450 mediated interactions involving adefovir as an inhibitor or substrate with other medicinal products is low.

The pharmacokinetics of adefovir have been evaluated in healthy adult volunteers following multiple dose administration of adefovir dipivoxil (10 mg once daily) in combination with lamivudine (100 mg once daily) (N=18), trimethoprim/sulfamethoxazole (160/800 mg twice daily) (N=18), acetaminophen (1000 mg four times daily) (N=20), ibuprofen (800 mg three times daily) (N=18), and enteric coated didanosine (400 mg) (N=21). The pharmacokinetics of adefovir have also been evaluated in post-liver transplantation patients following multiple dose administration of adefovir dipivoxil (10 mg once daily) in combination with tacrolimus (N=16). The pharmacokinetics of adefovir have been evaluated in healthy volunteers following single dose pegylated interferon α-2a (PEG-IFN) (180 microg) (N=15).

Adefovir did not alter the pharmacokinetics of lamivudine, trimethoprim/sulfamethoxazole, acetaminophen, ibuprofen, enteric coated didanosine (didanosine EC), or tacrolimus. The evaluation of the effect of adefovir on the pharmacokinetics of pegylated interferon α-2a was inconclusive due to the high variability of pegylated interferon alpha-2a.

The pharmacokinetics of adefovir were unchanged when adefovir dipivoxil was coadministered with lamivudine, trimethoprim/sulfamethoxazole, acetaminophen, didanosine EC, tacrolimus (based on cross study comparison), and pegylated interferon α-2a. When adefovir dipivoxil was coadministered with ibuprofen (800 mg three times daily) increases in adefovir Cmax (33%), AUC (23%) and urinary recovery were observed. This increase appears to be due to higher oral bioavailability, not a reduction in renal clearance of adefovir.

Apart from lamivudine, trimethoprim/sulfamethoxazole, and acetaminophen, the effects of coadministration of adefovir dipivoxil with drugs that are excreted renally, or other drugs known to affect renal function have not been evaluated.

The effect of adefovir on cyclosporine concentrations is not known.

No drug interaction studies have been performed in adolescent patients 12 to less than 18 years of age.

Special Populations

Gender

The pharmacokinetics of adefovir were similar in male and female patients.

Race

The pharmacokinetics of adefovir have been shown to be comparable in Caucasians and Asians. Pharmacokinetic data are not available for other racial groups.

Geriatric Patients

Pharmacokinetic studies have not been conducted in the elderly.

Pediatric Patients

The pharmacokinetics of adefovir were assessed from drug plasma concentrations in 53 HBeAg positive hepatitis B pediatric patients with compensated liver disease. The exposure of adefovir following a 48 week daily treatment with adefovir dipivoxil 10 mg tablet in pediatric patients 12 to less than 18 years of age (Cmax = 23.3 ng/mL and AUC0–24 = 248.8 ng∙h/mL) was comparable to that observed in adult patients.

Renal Impairment

In adults with moderately or severely impaired renal function or with end-stage renal disease (ESRD) requiring hemodialysis, Cmax, AUC, and half-life (T1/2) were increased compared to adults with normal renal function. It is recommended that the dosing interval of adefovir dipivoxil be modified in these patients [See Dosage and Administration (2.2)].

The pharmacokinetics of adefovir in non-chronic hepatitis B patients with varying degrees of renal impairment are described in Table 3. In this study, subjects received a 10 mg single dose of adefovir dipivoxil.

Table 3 Pharmacokinetic Parameters (Mean ± SD) of Adefovir in Patients with Varying Degrees of Renal Function
Renal Function Group | Unimpaired | Mild | Moderate | Severe
Baseline creatinine clearance (mL/min) | >80 (N=7) | 50 to 80 (N=8) | 30 to 49 (N=7) | 10 to 29 (N=10)
Cmax (ng/mL) | 17.8 ± 3.22 | 22.4 ± 4.04 | 28.5 ± 8.57 | 51.6 ± 10.3
AUC 0–∞ (ng∙h/mL) | 201 ± 40.8 | 266 ± 55.7 | 455 ± 176 | 1240 ± 629
CL/F (mL/min) | 469 ± 99.0 | 356 ± 85.6 | 237 ± 118 | 91.7 ± 51.3
CLrenal (mL/min) | 231 ± 48.9 | 148 ± 39.3 | 83.9 ± 27.5 | 37.0 ± 18.4

A four-hour period of hemodialysis removed approximately 35% of the adefovir dose. The effect of peritoneal dialysis on adefovir removal has not been evaluated.

The pharmacokinetics of adefovir have not been studied in adolescent patients with renal dysfunction [See Use in Specific Populations (8.4)].

Hepatic Impairment

The pharmacokinetics of adefovir following a 10 mg single dose of adefovir dipivoxil have been studied in non-chronic hepatitis B patients with hepatic impairment. There were no substantial alterations in adefovir pharmacokinetics in patients with moderate and severe hepatic impairment compared to unimpaired patients. No change in adefovir dipivoxil dosing is required in patients with hepatic impairment.

12.4 Microbiology

Mechanism of Action

Adefovir is an acyclic nucleotide analog of adenosine monophosphate which is phosphorylated to the active metabolite adefovir diphosphate by cellular kinases. Adefovir diphosphate inhibits HBV DNA polymerase (reverse transcriptase) by competing with the natural substrate deoxyadenosine triphosphate and by causing DNA chain termination after its incorporation into viral DNA. The inhibition constant (Ki) for adefovir diphosphate for HBV DNA polymerase was 0.1 microM. Adefovir diphosphate is a weak inhibitor of human DNA polymerases α and γ with Ki values of 1.18 microM and 0.97 microM, respectively.

Antiviral Activity

The concentration of adefovir that inhibited 50% of viral DNA synthesis (EC50) in HBV transfected human hepatoma cell lines ranged from 0.2 to 2.5 microM. The combination of adefovir with lamivudine in cell culture was not antagonistic.

Resistance

Clinical isolates with genotypic changes conferring reduced susceptibility in cell culture to nucleoside analog reverse transcriptase inhibitors for the treatment of HBV infection have been observed. Long-term resistance analyses performed by genotyping samples from all adefovir dipivoxil-treated patients with detectable serum HBV DNA demonstrated that amino acid substitutions rtN236T and rtA181T/V have been observed in association with adefovir resistance. In cell culture, the rtN236T substitution demonstrated 4- to 14-fold, the rtA181V substitution 2.5- to 4.2-fold, and the rtA181T substitution 1.3- to 1.9-fold reduced susceptibility to adefovir.

In HBeAg-positive nucleoside-naïve patient isolates (Study GS-98-437, N=171), no adefovir resistance-associated substitutions were observed at Week 48. Sixty-five patients continued on long term treatment after a median duration on adefovir dipivoxil of 235 weeks (range 110 to 279 weeks). Isolates from 16 of 38 (42%) patients developed adefovir resistance-associated substitutions in the setting of virologic failure (confirmed increase of at least 1 log10 HBV DNA copies/mL above nadir or never suppressed below 10^3 copies/mL). The substitutions included rtN236T (N=2), rtA181V (N=4), rtA181T (N=3), rtA181T+rtN236T (N=5), and rtA181V+rtN236T (N=2). In HBeAg-negative nucleoside-naïve patients (Study GS-98-438), isolates from 30 patients were identified with adefovir resistance-associated substitutions with a cumulative probability of 0%, 3%, 11%, 19%, and 30% at 48, 96, 144, 192, and 240 weeks, respectively. Of those 30 patients, 22 had a confirmed increase of at least 1 log10 HBV DNA copies/mL above nadir or never achieved HBV DNA levels below 10^3 copies/mL; an additional 8 patients had adefovir resistance-associated substitutions without virologic failure. In addition, the long term (4 to 5 years) development of resistance to adefovir dipivoxil was significantly lower in patients who had serum HBV DNA below the limit of quantification (less than 1,000 copies/mL) at Week 48 as compared to patients who had serum HBV DNA above 1,000 copies/mL at Week 48.

In an open-label study of pre- and post-liver transplantation patients (Study GS-98-435), isolates from 129 patients with clinical evidence of lamivudine-resistant hepatitis B virus at baseline were evaluated for adefovir resistance-associated substitutions. The incidence of adefovir resistance-associated (rtN236T or rtA181T/V) substitutions was 0% at 48 weeks. Isolates from four patients developed the rtN236T substitution after 72 weeks of adefovir dipivoxil therapy. Development of the rtN236T substitution was associated with serum HBV DNA rebound. All 4 patients who developed the rtN236T substitution in their HBV had discontinued lamivudine therapy before the development of genotypic resistance and all 4 lost the lamivudine resistance-associated substitutions present at baseline. In a study of 35 HIV/HBV co-infected patients with lamivudine-resistant HBV (Study 460i) who added adefovir dipivoxil to lamivudine, no adefovir resistance-associated substitutions were observed in HBV isolates from 15/35 patients tested up to 144 weeks of therapy.

Clinical resistance in pediatric patients

In a Phase 3 pediatric Study GS-US-103-518, HBV isolates from 49 of 56 pediatric subjects (aged 12 to 17 years) had serum HBV DNA greater than 169 copies/mL and were evaluated for adefovir resistance-associated substitutions. rtN236T and/or rtA181V adefovir resistance-associated substitutions were not observed at Week 48. However, the rtA181T substitution was present in baseline and Week 48 isolates from 2 pediatric patients.

Cross-resistance

Recombinant HBV variants containing lamivudine-resistance-associated substitutions (rtL180M, rtM204I, rtM204V, rtL180M + rtM204V, rtV173L + rtL180M + rtM204V) were susceptible to adefovir in cell culture. Adefovir dipivoxil has also demonstrated anti-HBV activity (median reduction in serum HBV DNA of 4.1 log10 copies/mL) in patients with HBV containing lamivudine-resistance-associated substitutions (Study 435). Adefovir also demonstrated in cell culture activity against HBV variants with entecavir resistance-associated substitutions (rtT184G, rtS202I, rtM250V). HBV variants with DNA polymerase substitutions rtT128N and rtR153Q or rtW153Q associated with resistance to hepatitis B virus immunoglobulin were susceptible to adefovir in cell culture.

HBV variants expressing the adefovir resistance-associated substitution rtN236T showed no change in susceptibility to entecavir in cell culture, and a 2- to 3-fold decrease in lamivudine susceptibility. HBV mutants with the adefovir resistance-associated substitution rtA181V showed a range of decreased susceptibilities to lamivudine of 1- to 14-fold and a 12-fold decrease in susceptibility to entecavir.

HBV isolates expressing rtA181T, rtA181V, or rtN236T single substitutions that are associated with resistance to adefovir had less than 2-fold changes in EC50 values to tenofovir and tenofovir alafenamide. However, the HBV isolate expressing the rtA181V plus rtN236T double substitutions exhibited reduced susceptibility to tenofovir (2.8-fold) and tenofovir alafenamide (3.7-fold). The clinical relevance of these substitutions is not known.

In patients whose HBV expressed the rtA181V substitution (N=2) or the rtN236T substitution (N=3), a reduction in serum HBV DNA of 2.4 to 3.1 and 2.0 to 5.1 log10 copies/mL, respectively, was observed when treatment with lamivudine was added to treatment with adefovir dipivoxil.

13 NONCLINICAL TOXICOLOGY

13.1 Carcinogenesis, Mutagenesis, Impairment of Fertility

Long-term oral carcinogenicity studies of adefovir dipivoxil in mice and rats were carried out at exposures up to approximately 10 times (mice) and 4 times (rats) those observed in humans at the therapeutic dose for HBV infection. In both mouse and rat studies, adefovir dipivoxil was negative for carcinogenic findings. Adefovir dipivoxil was mutagenic in the in vitro mouse lymphoma cell assay (with or without metabolic activation). Adefovir induced chromosomal aberrations in the in vitro human peripheral blood lymphocyte assay without metabolic activation. Adefovir dipivoxil was not clastogenic in the in vivo mouse micronucleus assay and adefovir was not mutagenic in the Ames bacterial reverse mutation assay using S. typhimurium and E. coli strains in the presence or absence of metabolic activation. In reproductive toxicology studies, no evidence of impaired fertility was seen in male or female rats at systemic exposure approximately 19 times that achieved in humans at the therapeutic dose.

13.2 Animal Toxicology and/or Pharmacology

Renal tubular nephropathy characterized by histological alterations and/or increases in BUN and serum creatinine was the primary dose-limiting toxicity associated with administration of adefovir dipivoxil in animals. Nephrotoxicity was observed in animals at systemic exposures approximately 3 to 10 times higher than those in humans at the recommended therapeutic dose of 10 mg/day.

14 CLINICAL STUDIES

14.1 Studies 437 and 438 (Pivotal Studies)

HBeAg-Positive Chronic Hepatitis B

Study 437 was a randomized, double-blind, placebo-controlled, three-arm study in patients with HBeAg-positive chronic hepatitis B that allowed for a comparison between placebo and adefovir dipivoxil. The median age of patients was 33 years. Seventy-four percent were male, 59% were Asian, 36% were Caucasian, and 24% had prior interferon-α treatment. At baseline, patients had a median total Knodell Histology Activity Index (HAI) score of 10, a median serum HBV DNA level as measured by the Roche Amplicor Monitor polymerase chain reaction (PCR) assay (LLOQ = 1000 copies/mL) of 8.36 log10 copies/mL and a median ALT level of 2.3 times the upper limit of normal.

HBeAg-Negative (Anti-HBe Positive/HBV DNA Positive) Chronic Hepatitis B

Study 438 was a randomized, double-blind, placebo-controlled study in patients who were HBeAg-negative at screening, and anti-HBe positive. The median age of patients was 46 years. Eighty-three percent were male, 66% were Caucasian, 30% were Asian and 41% had prior interferon-α treatment. At baseline, the median total Knodell HAI score was 10, the median serum HBV DNA level as measured by the Roche Amplicor Monitor PCR assay (LLOQ = 1000 copies/mL) was 7.08 log10 copies/mL, and the median ALT was 2.3 times the upper limit of normal.

The primary efficacy endpoint in both studies was histological improvement at Week 48; results of which are shown in Table 4.

Table 4 Histological Response at Week 48 [Intent-to-Treat population (patients with ≥1 dose of study drug) with assessable baseline biopsies.]
 | Study 437 |  | Study 438
 | Adefovir Dipivoxil 10 mg (N=168) | Placebo (N=161) | Adefovir Dipivoxil 10 mg (N=121) | Placebo (N=57)
Improvement [Histological improvement defined as ≥2 point decrease in the Knodell necro-inflammatory score with no worsening of the Knodell fibrosis score.] | 53% | 25% | 64% | 35%
No Improvement | 37% | 67% | 29% | 63%
Missing/Unassessable Data | 10% | 7% | 7% | 2%

Table 5 illustrates the changes in Ishak Fibrosis Score by treatment group.

Table 5 Changes in Ishak Fibrosis Score at Week 48
 | Study 437 |  | Study 438
Number of Adequate Biopsy Pairs | Adefovir Dipivoxil 10 mg (N=152) | Placebo (N=149) | Adefovir Dipivoxil 10 mg (N=113) | Placebo (N=56)
Ishak Fibrosis Score Improved [Change of 1 point or more in Ishak Fibrosis Score.] | 34% | 19% | 34% | 14%
Unchanged | 55% | 60% | 62% | 50%
Worsened | 11% | 21% | 4% | 36%

At Week 48, improvement was seen with respect to mean change in serum HBV DNA (log10 copies/mL), normalization of ALT, and HBeAg seroconversion as compared to placebo in patients receiving adefovir dipivoxil (Table 6).

Table 6 Change in Serum HBV DNA, ALT Normalization, and HBeAg Seroconversion at Week 48
 | Study 437 |  | Study 438
 | Adefovir Dipivoxil 10 mg (N=171) | Placebo (N=167) | Adefovir Dipivoxil 10 mg (N=123) | Placebo (N=61)
Mean change ± SD in serum HBV DNA from baseline (log10 copies/mL) | –3.57 ± 1.64 | –0.98 ± 1.32 | –3.65 ± 1.14 | –1.32 ± 1.25
ALT normalization | 48% | 16% | 72% | 29%
HBeAg seroconversion | 12% | 6% | NA [Patients with HBeAg-negative disease cannot undergo HBeAg seroconversion.] | NA

Treatment Beyond 48 Weeks

In Study 437, continued treatment with adefovir dipivoxil to 72 weeks resulted in continued maintenance of mean reductions in serum HBV DNA observed at Week 48. An increase in the proportion of patients with ALT normalization was also observed in Study 437. The effect of continued treatment with adefovir dipivoxil on seroconversion is unknown.

In Study 438, patients who received adefovir dipivoxil during the first 48 weeks were re-randomized in a blinded manner to continue on adefovir dipivoxil or receive placebo for an additional 48 weeks. At Week 96, 50 of 70 (71%) of patients who continued treatment with adefovir dipivoxil had undetectable HBV DNA levels (less than 1000 copies/mL), and 47 of 64 (73%) of patients had ALT normalization. HBV DNA and ALT levels returned towards baseline in most patients who stopped treatment with adefovir dipivoxil.

From 141 eligible patients, there were 125 (89%) patients in Study 438 who chose to continue adefovir dipivoxil for up to 192 weeks or 240 weeks (4 years or 5 years). As these patients had already received adefovir dipivoxil for at least 48 weeks and appeared to be experiencing a benefit, they are not necessarily representative of patients initiating adefovir dipivoxil. Of these patients, 89/125 (71%) and 47/70 (67%) had an undetectable HBV DNA level (less than 1000 copies/mL) at Week 192 and Week 240, respectively. Of the patients who had an elevated ALT at baseline, 77/104 (74%) and 42/64 (66%) had a normal ALT at Week 192 and Week 240, respectively. Six (5%) patients experienced HBsAg loss.

14.2 Study 435 (Pre- and Post-Liver Transplantation Patients)

Adefovir dipivoxil was also evaluated in an open-label, uncontrolled study of 467 chronic hepatitis B patients pre- (N=226) and post- (N=241) liver transplantation with clinical evidence of lamivudine-resistant hepatitis B virus (Study 435). At baseline, 60% of pre-liver transplantation patients were classified as Child-Pugh-Turcotte score of Class B or C. The median baseline HBV DNA as measured by the Roche Amplicor Monitor PCR assay (LLOQ = 1000 copies/mL) was 7.4 and 8.2 log10 copies/mL, and the median baseline ALT was 1.8 and 2.0 times the upper limit of normal in pre- and post-liver transplantation patients, respectively. Results of this study are displayed in Table 7. Treatment with adefovir dipivoxil resulted in a similar reduction in serum HBV DNA regardless of the patterns of lamivudine-resistant HBV DNA polymerase mutations at baseline. The significance of the efficacy results listed in Table 7 as they relate to clinical outcomes is not known.

Table 7 Efficacy in Pre- and Post-Liver Transplantation Patients at Week 48
Efficacy Parameter [Data are missing for 29% (HBV DNA) and 37% to 45% (CPT Score, Normalization of ALT, Albumin, Bilirubin, and PT) of total patients enrolled in the study.] | Pre-Liver Transplantation (N=226) | Post-Liver Transplantation (N=241)
Mean change ± SD in HBV DNA from baseline (log10 copies/mL) | –3.7 ± 1.6 (N=117) | –4.0 ± 1.6 (N=164)
Proportion with undetectable HBV DNA (< 1000 copies/mL) [Denominator is the number of patients with serum HBV DNA ≥1000 copies/mL at baseline using the Roche Amplicor Monitor PCR Assay (LLOQ = 1000 copies/mL) and non-missing value at Week 48.] | 77/109 (71%) | 64/159 (40%)
Stable or improved Child-Pugh-Turcotte score | 86/90 (96%) | 107/115 (93%)
Normalization of: [Denominator is patients with abnormal values at baseline and non-missing value at Week 48.]
ALT | 61/82 (74%) | 56/110 (51%)
Albumin | 43/54 (80%) | 21/26 (81%)
Bilirubin | 38/68 (58%) | 29/38 (76%)
Prothrombin time | 39/46 (85%) | 5/9 (56%)

14.3 Study 461 (Clinical Evidence of Lamivudine Resistance)

In Study 461, a double-blind, active controlled study in 59 chronic hepatitis B patients with clinical evidence of lamivudine-resistant hepatitis B virus, patients were randomized to receive either adefovir dipivoxil monotherapy or adefovir dipivoxil in combination with lamivudine 100 mg or lamivudine 100 mg alone. At Week 48, the mean ± SD decrease in serum HBV DNA as measured by the Roche Amplicor Monitor PCR assay (LLOQ = 1000 copies/mL) was 4.00 ± 1.41 log10 copies/mL for patients treated with adefovir dipivoxil and 3.46 ± 1.10 log10 copies/mL for patients treated with adefovir dipivoxil in combination with lamivudine. There was a mean decrease in serum HBV DNA of 0.31 ± 0.93 log10 copies/mL in patients receiving lamivudine alone. ALT normalized in 47% of patients treated with adefovir dipivoxil, in 53% of patients treated with adefovir dipivoxil in combination with lamivudine, and 5% of patients treated with lamivudine alone. The significance of these findings as they relate to clinical outcomes is not known.

14.4 Study 518 (Pediatric Study)

Study 518 was a double-blind, placebo-controlled, study in which 173 pediatric patients (ages 2 to less than 18 years) with chronic hepatitis B (CHB) infection and elevated ALT were randomized 2:1 (115 receiving adefovir dipivoxil and 58 receiving placebo). Randomization was stratified by prior treatment and age 2 to less than 7 years old (cohort 1), 7 to less than 12 years old (cohort 2), and 12 to less than 18 years old (cohort 3). All patients in cohort 3 received 10 mg tablet formulation; all patients in cohorts 1 and 2 received an investigational suspension formulation (0.3 mg/kg/day cohort 1, 0.25 mg/kg/day cohort 2) once daily. The primary efficacy endpoint was HBV DNA less than 1000 copies/mL plus normalization of ALT at the end of Week 48.

In cohort 3 (N=83), significantly more patients treated with adefovir dipivoxil achieved the primary efficacy endpoint at the end of 48 weeks of blinded treatment (23%) when compared to placebo-treated patients (0%). The proportion of patients from cohorts 1 and 2 who responded to treatment with adefovir dipivoxil was not statistically significant when compared to the placebo arm, although the adefovir plasma concentrations in these patients were comparable to those observed in older patients. Overall, 22 of 115 (19%) of pediatric patients who received adefovir dipivoxil versus 1 of 58 (2%) of placebo treated patients responded to treatment by Week 48 [See Adverse Reactions (6.3), Use In Specific Populations (8.4) and Clinical Pharmacology (12.3, 12.4)].

16 HOW SUPPLIED / STORAGE AND HANDLING

Adefovir Dipivoxil Tablets are white to off-white, round, flat-faced bevelled edge tablets, engraved “APO” on one side, “A10” on the other side. They are supplied as follows:

Bottles of 30s (NDC-60505-3947-3)

STORAGE AND HANDLING

Store in original container at 20°C to 25°C (68°F to 77°F); excursions permitted from 15°C to 30°C (59°F to 86°F) [see USP Controlled Room Temperature].

Do not use if seal over bottle opening is broken or missing.

17 PATIENT COUNSELING INFORMATION

Advise the patient to read the FDA-approved patient labeling (Patient Information).

- Inform patients of the potential risks and benefits of adefovir dipivoxil tablets and of alternative modes of therapy.
- Instruct patients to:
  - Follow a regular dosing schedule to avoid missing doses.
  - Immediately report any severe abdominal pain, muscle pain, yellowing of the eyes, dark urine, pale stools, and/or loss in appetite.
  - Inform their doctor or pharmacist if they develop any unusual symptom(s), or if any known symptom persists or worsens.

- Advise patients that:
  - The optimal duration of adefovir dipivoxil tablets treatment and the relationship between treatment response and long-term outcomes such as hepatocellular carcinoma or decompensated cirrhosis are not known.
  - Patients should not discontinue adefovir dipivoxil tablets without first informing their physician [See Warnings and Precautions (5.1)].
  - Routine laboratory monitoring and follow-up with a physician is important during adefovir dipivoxil therapy.
  - Obtaining HIV antibody testing prior to starting adefovir dipivoxil tablets is important [See Warnings and Precautions (5.3)].
  - Adefovir dipivoxil tablets should not be administered concurrently with ATRIPLA or COMPLERA or STRIBILD or TRUVADA or VIREAD [See Warnings and Precautions (5.5)].
  - Lamivudine-resistant patients should use adefovir dipivoxil tablets in combination with lamivudine and not as adefovir dipivoxil tablets monotherapy [See Warnings and Precautions. (5.6)].

- Inform patients that there is an antiretroviral pregnancy registry to monitor fetal outcomes of pregnant women exposed to adefovir dipivoxil [see Use in Specific Populations (8.1)].

All registered trademarks in this document are the property of their respective owners.

APOTEX INC.
Adefovir Dipivoxil Tablets
10 mg

Manufactured By: | Manufactured For:
Apotex Inc. | Apotex Corp.
Toronto, Ontario | Weston, Florida
Canada M9L 1T9 | USA 33326

Revised: January 2019

Rev. 3

PATIENT INFORMATION

Adefovir Dipivoxil Tablets
(a def’ oh vir dye" piv ox’ il)

Read this Patient Information before you start taking adefovir dipivoxil tablets and each time you get a refill. There may be new information. This information does not take the place of talking with your doctor about your medical condition or your treatment.

What is the most important information I should know about adefovir dipivoxil tablets?

Adefovir dipivoxil tablets can cause serious side effects, including:

- Worsening of hepatitis B infection. Your hepatitis B (HBV) infection may become worse (flare-up) if you take adefovir dipivoxil tablets and then stop taking it. A “flare-up” is when your HBV infection suddenly returns in a worse way than before.
  - Do not run out of adefovir dipivoxil tablets. Refill your prescription or talk to your doctor before your adefovir dipivoxil tablets is all gone.
  - Do not stop taking adefovir dipivoxil tablets without first talking with your doctor.
  - If you stop taking adefovir dipivoxil tablets, your doctor will need to check your health often and do blood tests regularly to check your HBV infection for at least several months.

- Adefovir dipivoxil tablets may cause severe kidney problem. Severe kidney problems can happen in anyone who takes adefovir dipivoxil tablets, but certain people may have a higher risk of severe kidney problems with adefovir dipivoxil tablets, including:
  - people who already have kidney problems or are at an increased risk for kidney problems, and
  - people who take certain medicines that can cause kidney problems. Ask your doctor whether any of the medicines you currently take can cause kidney problems.

Your doctor should do blood tests to check your kidney function during treatment with adefovir dipivoxil tablets.

If you have kidney problems before you start taking adefovir dipivoxil tablets your doctor may change your dose of adefovir dipivoxil tablets. If you develop kidney problems during treatment, your doctor may need to change your dose of adefovir dipivoxil tablets or may stop your treatment.

- HIV resistance. Your doctor may test you for HIV-1 infection before your start adefovir dipivoxil tablets. If you have both HBV and HIV-1 and you only take adefovir dipivoxil tablets, the HIV-1 virus may develop resistance and become harder to treat.
- Build-up of acid in your blood (lactic acidosis). Lactic acidosis can happen in some people who take adefovir dipivoxil tablets. Lactic acidosis is a serious medical emergency that can lead to death.

Call your doctor right away if you get any of the following symptoms which could be signs of lactic acidosis:

-
  - feel very weak or tired
  - unusual (not normal) muscle pain
  - trouble breathing
  - stomach pain with nausea and vomiting
  - feel cold, especially in your arms and legs
  - feel dizzy or lightheaded
  - have a fast or irregular heartbeat

- Severe liver problems. In rare cases, severe liver problems can happen that lead to death. Call your doctor right away if you get any of the following signs or symptoms of liver problems.
  - your skin or the white part of your eyes turns yellow (jaundice).
  - dark or “tea-colored” urine
  - light-colored stools (bowel movements)
  - nausea
  - loss of appetite for several days or longer
  - pain, aching, or tenderness on the right side of your stomach-area

You may be more likely to get lactic acidosis or serious liver problems if you are female, are very overweight (obese), or have been taking nucleoside analog medicines for a long time.

What are adefovir dipivoxil tablets?

Adefovir dipivoxil tablets are a medicine used to treat people 12 years of age and older with chronic (long-lasting) infections with active hepatitis B virus.

Adefovir dipivoxil tablets is not for use in children under 12 years of age.

- Adefovir dipivoxil tablets may lower the amount of hepatitis B virus (HBV) in your body.
- Adefovir dipivoxil tablets may improve the condition of your liver.

Who should not take adefovir dipivoxil tablets?

Do not take adefovir dipivoxil tablets if you are allergic to any of the ingredients in adefovir dipivoxil tablets. See the end of this leaflet for a complete list of all the ingredients in adefovir dipivoxil tablets.

What should I tell my healthcare provide before taking adefovir dipivoxil tablets?

Before taking adefovir dipivoxil tablets, tell your doctor about all of your medical conditions, including if you:

- have or had kidney problems. Your dose and schedule of adefovir dipivoxil tablets may need to be changed.
- are pregnant or plan to become pregnant. It is not known if adefovir dipivoxil tablets will harm your unborn baby. Pregnancy Registry: There is a pregnancy registry for women who take adefovir dipivoxil tablets during pregnancy. The purpose of this registry is to collect information about the health of you and your baby. Talk with your doctor about how you can take part in this registry.
- are breastfeeding. It is not known if adefovir dipivoxil tablets passes into your breast milk. Talk with your doctor about the best way to feed your baby during treatment with adefovir dipivoxil tablets.

Tell your doctor about all the medicines you take, including prescription and over-the-counter medicines, vitamins, and herbal supplements. Some medicines may affect how adefovir dipivoxil tablets works, especially medicines that affect how your kidneys work. adefovir dipivoxil tablets can affect how your other medicines work. Your dose of adefovir dipivoxil tablets and the other medicines may need to be changed. Do not start a new medicine without telling your doctor. Your doctor can tell you if it is safe to take adefovir dipivoxil tablets with other medicines.

How should I take adefovir dipivoxil tablets?

- Take adefovir dipivoxil tablets exactly as your doctor tells you to take it.
- Your doctor will tell you how much adefovir dipivoxil tablets to take, and when and how often to take it.
- Do not change your dose or stop adefovir dipivoxil tablets without talking to your doctor. Your hepatitis may get worse if you change doses or stop.
- Take adefovir dipivoxil tablets at the same time each day that your doctor tells you, to avoid missing doses.
- Take adefovir dipivoxil tablets with or without food.
- Stay under the care of your doctor during treatment with adefovir dipivoxil tablets.
- When your adefovir dipivoxil tablets supply gets low, call your doctor or pharmacy for a refill. Do not run out of adefovir dipivoxil tablets.
- If you take too much adefovir dipivoxil tablets, call your doctor or go to the nearest hospital emergency room right away.
- It is not known how long you should take adefovir dipivoxil tablets. You and your doctor will need to decide when it is best for you to stop taking adefovir dipivoxil tablets. Some people get worsening of their hepatitis B infection when they stop taking adefovir dipivoxil tablets. See “What is the most important information I should know about adefovir dipivoxil tablets?”.

What are the possible side effects of adefovir dipivoxil tablets?

Adefovir dipivoxil tablets can cause serious side effects. See “What is the most important information I should know about adefovir dipivoxil tablets?”) The most common side effects of adefovir dipivoxil tablets are weakness, headache, stomach pain, and nausea.

These are not all the possible side effects of adefovir dipivoxil tablets. For more information, ask your doctor or pharmacist.

Call your doctor for advice about side effects. You may report side effects to FDA at 1-800-FDA-1088

How should I store adefovir dipivoxil tablets?

- Adefovir dipivoxil tablets should be stored at 20°C to 25°C (68°F to 77°F).
- Keep adefovir dipivoxil tablets in its original container.
- Do not use adefovir dipivoxil tablets if the seal over the bottle is broken or missing when you receive it.

Keep adefovir dipivoxil tablets and all medicines out of the reach of children.

General information about the safe and effective use of adefovir dipivoxil tablets:

Medicines are sometimes prescribed for purposes other than those listed in a Patient Information leaflet. Do not use HEPSERA for a condition for which it was not prescribed. Do not give HEPSERA to other people, even if they have the same symptoms that you have. It may harm them. If you would like more information, talk with your doctor. You can ask your doctor or pharmacist for information about HEPSERA that is written for health professionals.

What are the Ingredients of adefovir dipivoxil tablets?

Active Ingredient: adefovir dipivoxil

Inactive Ingredients: croscarmellose sodium, lactose monohydrate, magnesium stearate, starch and talc.

All registered trademarks in this document are the property of their respective owners.

APOTEX INC.
Adefovir Dipivoxil Tablets
10 mg

Manufactured By: | Manufactured For:
Apotex Inc. | Apotex Corp.
Toronto, Ontario | Weston, Florida
Canada M9L 1T9 | USA 33326

Revised: January 2019

Rev. 3

PACKAGE LABEL - PRINCIPAL DISPLAY PANEL - 10MG LABEL

APOTEX CORP. NDC 60505-3947-3

Adefovir Dipivoxil Tablets, 10 mg

30 tablets

Rx only

PACKAGE LABEL - PRINCIPAL DISPLAY PANEL - 10MG CARTON

APOTEX CORP. NDC 60505-3947-3

Adefovir Dipivoxil Tablets, 10 mg

30 tablets

Rx only